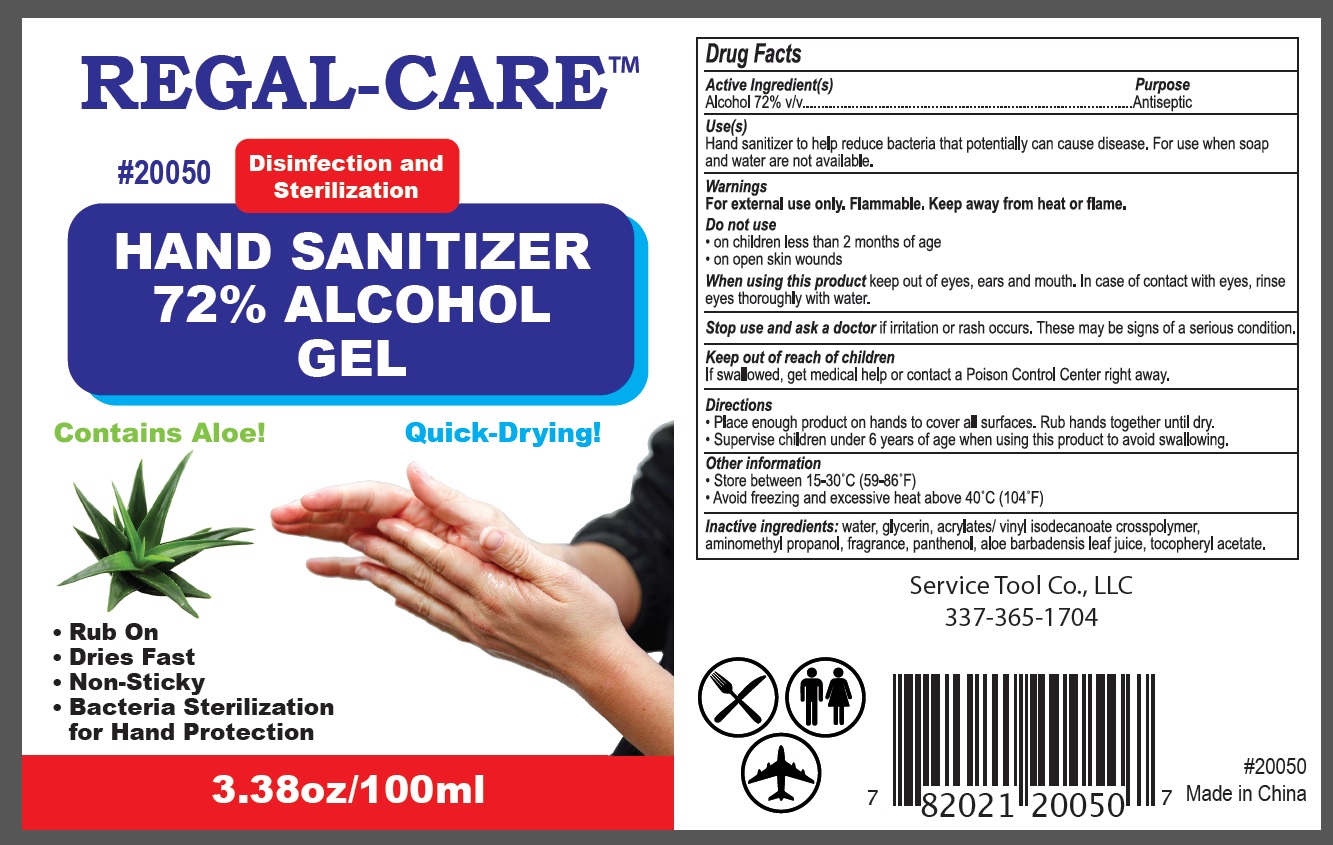 DRUG LABEL: REGAL CARE
NDC: 78710-072 | Form: GEL
Manufacturer: SERVICE TOOL COMPANY, L.L.C.
Category: otc | Type: HUMAN OTC DRUG LABEL
Date: 20200706

ACTIVE INGREDIENTS: ALCOHOL 72 mL/100 mL
INACTIVE INGREDIENTS: WATER; GLYCERIN; ACRYLATES/VINYL ISODECANOATE CROSSPOLYMER (10000 MPA.S NEUTRALIZED AT 0.5%); AMINOMETHYLPROPANOL; PANTHENOL; ALOE VERA LEAF; .ALPHA.-TOCOPHEROL ACETATE

Active Ingredient

Alcohol 72% v/v

Purpose

Antiseptic

Use

Hand Sanitizer to help reduce bacteria that potentially can cause disease. For use when soap and water are not available.

Warnings

For external use only. Flammable. Keep away from heat or flame

Do not use

- on children less than 2 months of age
- on open skin wounds

When using this product

keep out of eyes, ears, and mouth. In case of contact with eyes, rinse eyes thoroughly with water.

Stop use and ask a doctor

if irritation or rash occurs. These may be signs of a serious condition.

Keep out of reach of children.

If swallowed, get medical help or contact a Poison Control Center right away.

Directions

- Place enough product on hands to cover all surfaces. Rub hands together until dry.
- Supervise children under 6 years of age when using this product to avoid swallowing.

Other information

- Store between 15-30C (59-86F)
- Avoid freezing and excessive heat above 40C (104F)

Inactive ingredients

water, glycerin, acrylates/vinyl isodecanoate crosspolymer, aminomethylpropanol, fragrance, panthenol, aloe barbadensis leaf juice,tocopherol acetate.

Package Label - Principal Display Panel

NDC 78710-072-03

REGAL-CARETM

# 20050

Disinfection and Sterilization

HAND SANITIZER 72% ALCOHOL GEL

Contains Aloe!

Quick-Drying!

- Rub On
- Dries Fast
- Non-Sticky
- Bacteria Sterilization for Hand Protection

3.38oz/100ml